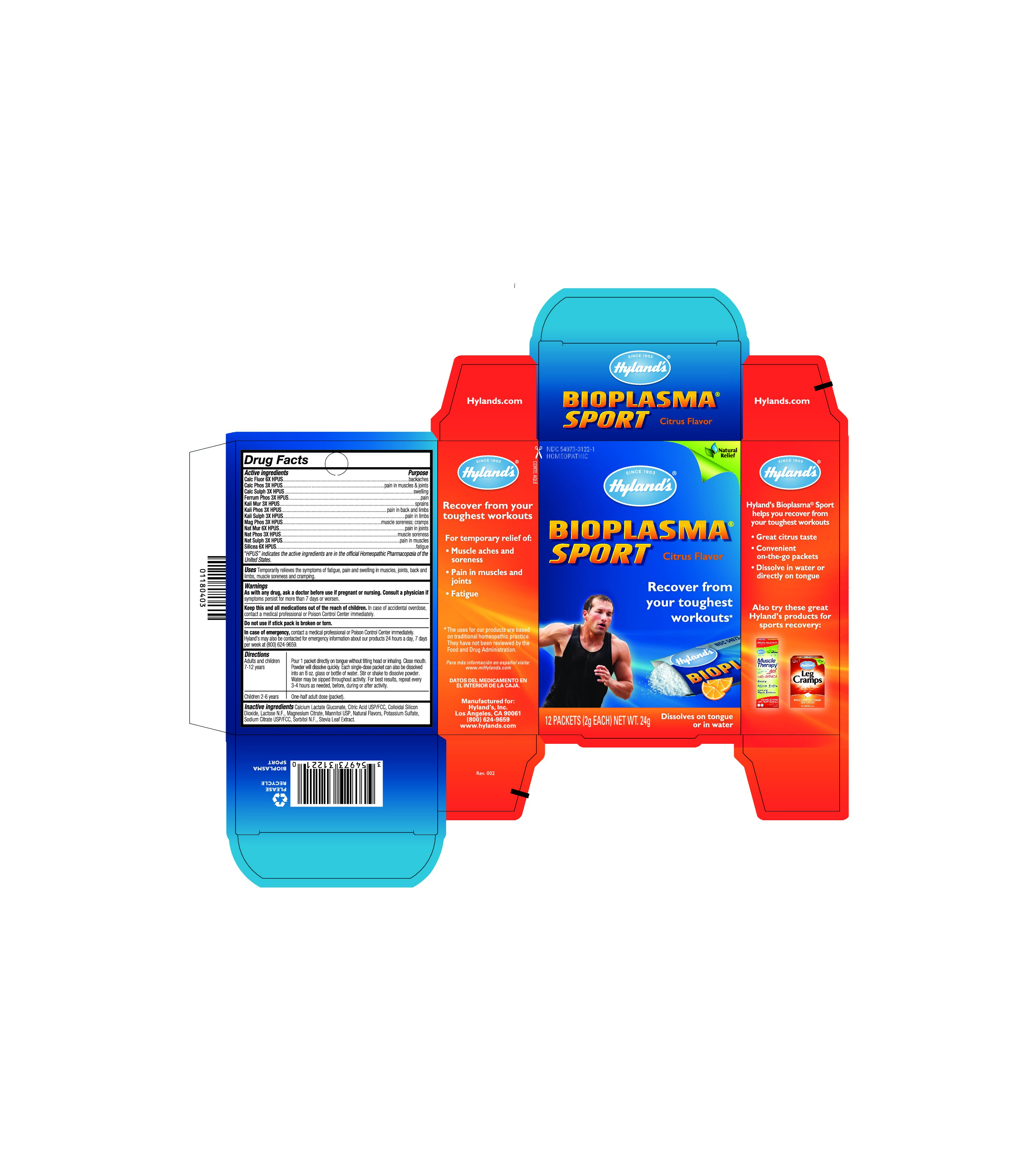 DRUG LABEL: BIOPLASMA SPORT WITH ELECTROLYTES
NDC: 54973-3122 | Form: POWDER
Manufacturer: Hyland's
Category: homeopathic | Type: HUMAN OTC DRUG LABEL
Date: 20180307

ACTIVE INGREDIENTS: CALCIUM FLUORIDE 6 [hp_X]/2 g; TRIBASIC CALCIUM PHOSPHATE 3 [hp_X]/2 g; CALCIUM SULFATE ANHYDROUS 3 [hp_X]/2 g; FERROSOFERRIC PHOSPHATE 3 [hp_X]/2 g; POTASSIUM CHLORIDE 3 [hp_X]/2 g; POTASSIUM PHOSPHATE, DIBASIC 3 [hp_X]/2 g; MAGNESIUM PHOSPHATE, DIBASIC TRIHYDRATE 3 [hp_X]/2 g; SODIUM CHLORIDE 6 [hp_X]/2 g; SODIUM PHOSPHATE, DIBASIC, HEPTAHYDRATE 3 [hp_X]/2 g; SODIUM SULFATE 3 [hp_X]/2 g; SILICON DIOXIDE 6 [hp_X]/2 g
INACTIVE INGREDIENTS: LACTOSE; CALCIUM CATION; ANHYDROUS CITRIC ACID; MAGNESIUM CATION; MANNITOL; SULFATE ION; SORBITOL; STEVIA REBAUDIUNA LEAF

BIOPLASMA® SPORT WITH ELECTROLYTES

Drug Facts

ACTIVE INGREDIENT

Active Ingredients | Purpose
Calc Fluor 6X HPUS | backaches
Calc Phos 3X HPUS | pain in muscles & joints
Calc Sulph 3X HPUS | swelling
Ferrum Phos 3X HPUS | pain
Kali Mur 3X HPUS | sprains
Kali Phos 3X HPUS | pain in back and limbs
Kali Sulph 3X HPUS | pain in limbs
Mag Phos 3X HPUS | muscle soreness; cramps
Nat Mur 6X HPUS | pain in joints
Nat Phos 3X HPUS | muscle soreness
Nat Sulph 3X HPUS | pain in muscles
Silicea 6X HPUS | fatigue

“HPUS” indicates that the active ingredients are in the official Homeopathic Pharmacopœia of the United States.

Uses

Temporarily relieves the symptoms of fatigue, pain and swelling in muscles,joints, back and limbs, muscle soreness and cramping.

Warnings

PREGNANCY OR BREAST FEEDING

As with any drug, ask a doctor before use if pregnant or nursing.

ASK DOCTOR

Consult a physician if symptoms persist for more than 7 days or worsen.

Do not use if stick pack is broken or torn.

KEEP OUT OF REACH OF CHILDREN

Keep this and all medications out of the reach of children. In case of accidental overdose contact a medical professional or Poison Control Center immediately.

In case of emergency, contact a medical proffessional or Poison Control Center immediately. Hyland's may be contacted 24 hours a day, 7 days a week at 800/624-9659.

Directions

Adults and children 7-12 years: Pour 1 packet directly on tongue without tilting head or inhaling. Close mouth. Powder will dissolve quickly. Each single-dose packet can also be dissolved into an 8 oz glass or bottle of water. Stir or shake to dissolve powder. Water may be sipped throughout activity. For best results, repeat every 3-4 hours as needed, before during or after activity. Children Ages 2-6 years: One-Half adult dose (packet).

Inactive Ingredients

Calcium lactate gluconate, citric acid USP/FCC, colloidal silicon dioxide, lactose NF C/S, magnesium citrate, mannitol USP, natural flavors, potassium sulfate, sodium citrate USP/FCC, sorbitol NF, stevia leaf extract.

Questions?

800/624-9659

PRINCIPAL DISPLAY PANEL - 12 Packet Carton

NDC 54973-3122-1
HOMEOPATHIC

Natural

Relief

Hyland's®

BIOPLASMA®
SPORT Citrust Flavor

Recover from
your toughest

workouts*

12 PACKETS (2g EACH) NET WT.24g

Dissolves on tongue or in water